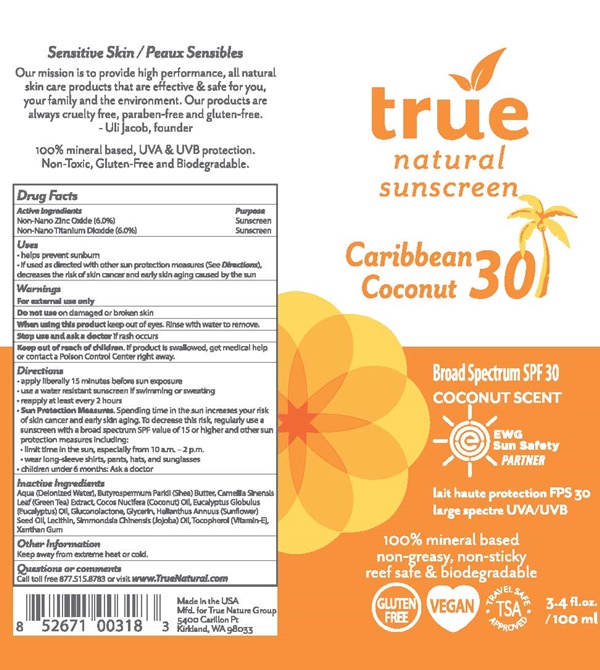 DRUG LABEL: true natural Caribbean Coconut 30
NDC: 76245-018 | Form: LOTION
Manufacturer: True Nature Group, Inc.
Category: otc | Type: HUMAN OTC DRUG LABEL
Date: 20170203

ACTIVE INGREDIENTS: ZINC OXIDE 6 g/100 mL; TITANIUM DIOXIDE 6 g/100 mL
INACTIVE INGREDIENTS: WATER; SHEA BUTTER; CAMELLIA SINENSIS FLOWER; COCONUT OIL; EUCALYPTUS OIL; GLUCONOLACTONE; SUNFLOWER OIL; LECITHIN, SUNFLOWER; JOJOBA OIL; .ALPHA.-TOCOPHEROL; XANTHAN GUM

true natural Caribbean Coconut - 018

Drug Facts Active Ingredients

Non- Nano Zinc Oxide (6%)

Non-Nano Titanium Dioxide (6%)

Purpose

Siuscreen

Uses

- helps prevent sunburn
- if used as directed with other sun protection measures (See Directions), decreases the risk of skin cancer and early skin aging caused by the sun

Warnings

For external use only

Do not use

on damaged or broken skin.

When using this product

keep out of eyes. Rinse with water to remove.

Stop use and ask a doctor

if rash occurs

Keep out of reach of children.

If product is swallowed, get medical help or contact a Poison Control Center right away.

Directions

- apply liberally 15 minutes before sun exposure
- use a water resistant sunscreen if swimming or sweating
- reapply at least every 2 hours
- Sun Protection Measures Spending time in the sun increases your risk of skin cancer and early skin aging. To decrease this risk, regularly use a sunscreen with a broad with a broad spectrum SPF value of 15 or higher and other sun protection measures including:
  - limit time in the sun, especially from 10 a.m. - 2 p.m.
  - wear long-sleeved shirts, pants, hats, and sunglasses
  - children under 6 months: Ask a doctor

Inactive Ingredients

Aqua (Delonized Water), Butyrospermum Parkii (Shea) Butter, Camellia Sinensis (Green Tea) Extract, Cocos Nucifera (Coconut Oil), Eucalptus Globulus (Eucalptus) Oil, Gluconolctone, Glycerin, Helianthus Annuus (Sunflower)Oil, Lecithin, Simmondsia Chinensis (Jojoba) Oil,Tocopherol (Vitamin-E), Xanthan Gum

Other Information

Keep away from extreme heat or cold.

Questions or comments

Call toll free 877.515.8783 or visit www.True.Natural.com

true natural Caribbean Coconut 30 product label

true

natural
sunscreen

Caribbean Coconut 30

Broad Spectrum SPF 30 COCONUT SCENT

EWG Sun Safety Partner

large spectre UVA/UVB

100% minera lbased
non-greasy, non-sticky
reef safe & biodegradable

GLUTEN FREE VEGAN TSA -TRAVEL SAFE APPROVED

3-4 fl oz./ 100 ml

Made in the USA

Mfd for True Nature Group
5400 Carillon Pt
Kirkland, WA 98033

Sensitive Skin

Our mission is to provide high performance, all natural skin care products that are effective & safe for you, your family and the environment. Our products are always cruelty free, paraben-free, and gluten-free.

UI Jacob, founder

100% mineral based, UVA & UVB protection
Non-Toxic, Gluten-Free and Biodegradable.